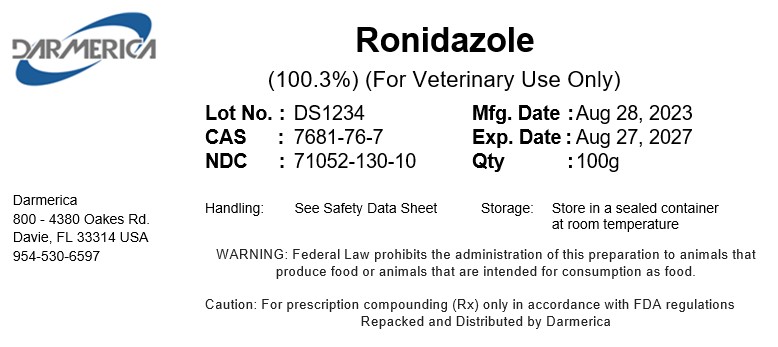 DRUG LABEL: Ronidazole
NDC: 71052-130 | Form: POWDER
Manufacturer: DARMERICA, LLC
Category: other | Type: BULK INGREDIENT - ANIMAL DRUG
Date: 20241223

ACTIVE INGREDIENTS: Ronidazole 1 kg/1 kg

Ronidazole